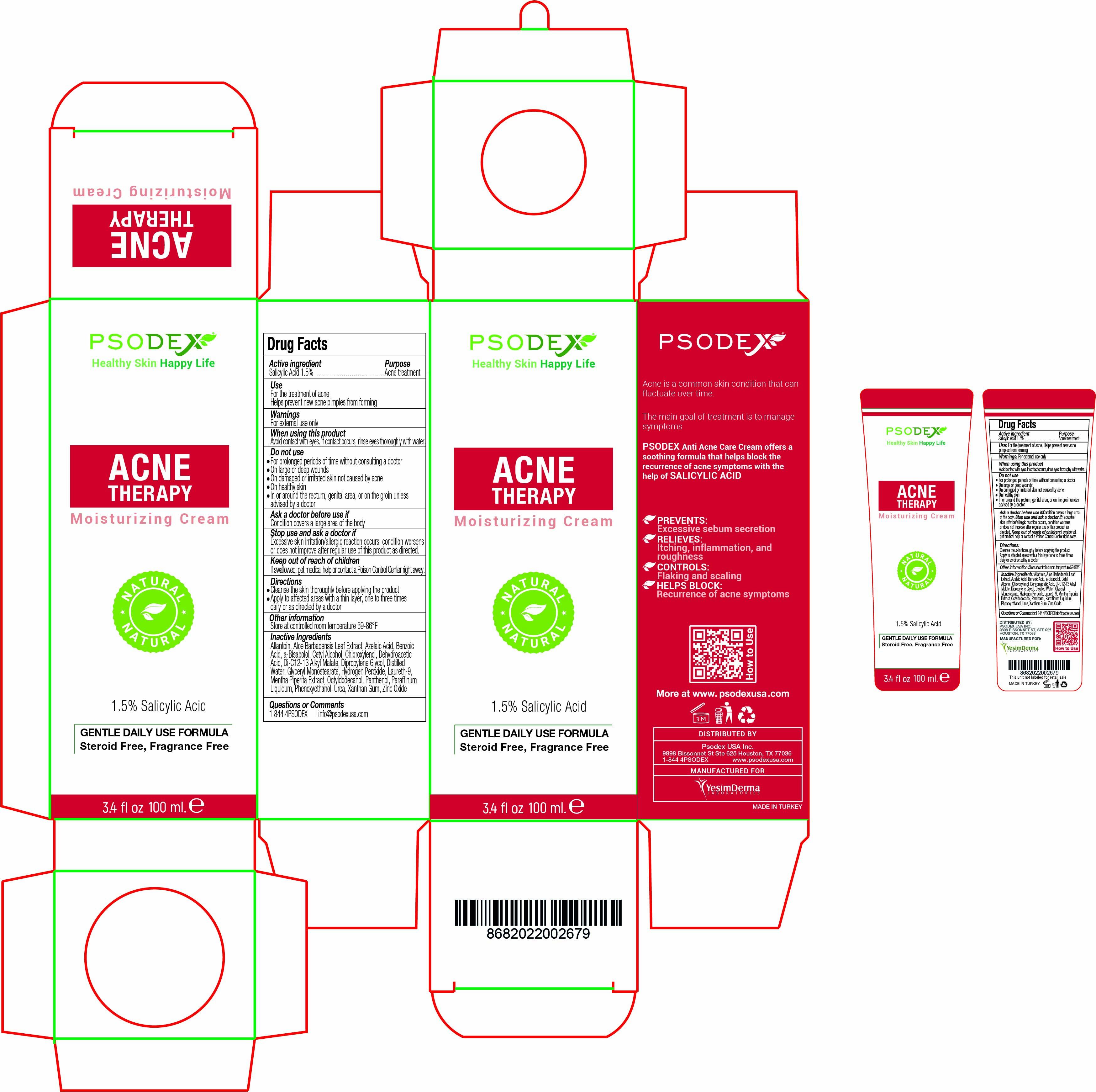 DRUG LABEL: Acne Therapy
NDC: 73503-008 | Form: CREAM
Manufacturer: PSODEX USA INC
Category: otc | Type: HUMAN OTC DRUG LABEL
Date: 20231221

ACTIVE INGREDIENTS: SALICYLIC ACID 1.5 g/100 mL
INACTIVE INGREDIENTS: LEVOMENOL 2 g/100 mL; PHENOXYETHANOL 0.5 g/100 mL; ALOE VERA LEAF 5 g/100 mL; POLIDOCANOL 3 g/100 mL; OCTYLDODECANOL 2 g/100 mL; HYDROGEN PEROXIDE 1 g/100 mL; UREA 5 g/100 mL; MENTHA PIPERITA LEAF 5 g/100 mL; PANTHENOL 1 g/100 mL; MINERAL OIL 5 g/100 mL; DEHYDROACETIC ACID 0.25 g/100 mL; CHLOROXYLENOL 0.5 g/100 mL; ZINC OXIDE 5 g/100 mL; XANTHAN GUM 0.3 g/100 mL; ALLANTOIN 2 g/100 mL; CETYL ALCOHOL 5 g/100 mL; GLYCERYL MONOSTEARATE 2 g/100 mL; DIPROPYLENE GLYCOL 0.2 g/100 mL; BENZOIC ACID 0.25 g/100 mL; DI-C12-13 ALKYL MALATE 2 g/100 mL; AZELAIC ACID 3 g/100 mL; WATER 43.5 mL/100 mL

Acne Therapy Moisturizing Cream

DESCRIPTION

Acne is a common skin condition that can fluctuate over time.

The main goal of treatment is to manage symptoms

PSODEX Anti Acne Care Cream offers a soothing formula that helps block the recurrence of acne symptoms with the help of SALICYLIC ACID

PREVENTS:
Excessive sebum secretion

RELIEVES:
Itching, inflammation, and roughness

CONTROLS:
Flaking and scaling

HELPS BLOCK:
Recurrence of acne symptoms

Active ingredient

Salicylic Acid 1.5%

Active ingredient

Salicylic Acid 1.5%

Inactive Ingredients

Allantoin, Aloe Barbadensis Leaf Extract, Azelaic Acid, Benzoic
Acid, a-Bisabolol, Cetyl Alcohol, Chloroxylenol, Dehydroacetic
Acid, Di-C12-13 Alkyl Malate, Dipropylene Glycol, Distilled
Water, Glyceryl Monostearate, Hydrogen Peroxide, Laureth-9,
Mentha Piperita Extract, Octyldodecanol, Panthenol, Paraffinum
Liquidum, Phenoxyethanol, Urea, Xanthan Gum, Zinc Oxide

Directions

- Cleanse the skin thoroughly before applying the product
- Apply to affected areas with a thin layer, one to three times daily or as directed by a doctor

Use

For the treatment of acne
Helps prevent new acne pimples from forming

INFORMATION FOR OWNERS/CAREGIVERS

DISTRIBUTED BY: Psodex USA Inc.

9898 Bissonnet St Ste 625 Houston, TX 77036

1-844 4PSODEX www.psodexusa.com

MANUFACTURED FOR

Yesim Derma Laboratories

Do not use

- For prolonged periods of time without consulting a doctor
- On large or deep wounds
- On damaged or irritated skin not caused by acne
- On healthy skin
- In or around the rectum, genital area, or on the groin unless advised by a doctor

Ask a doctor before use if

Condition covers a large area of the body

Stop use and ask a doctor if

Excessive skin irritation/allergic reaction occurs, condition worsens or does not improve after regular use of this product as directed.

Keep out of reach of children

If swallowed, get medical help or contact a Poison Control Center right away.

Questions or Comments

1 844 4PSODEX | info@psodexusa.com

Other information

Store at controlled room temperature 59-86°F

Warnings

For external use only

Purpose

Acne treatment

When using this product

Avoid contact with eyes. If contact occurs, rinse eyes thoroughly with water.